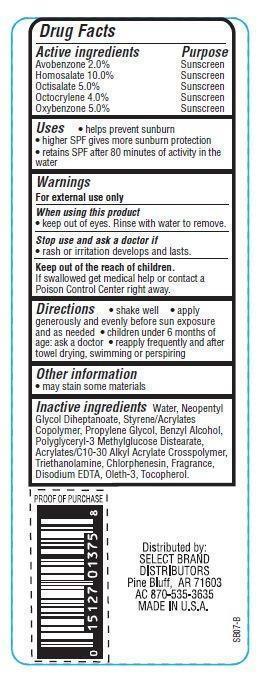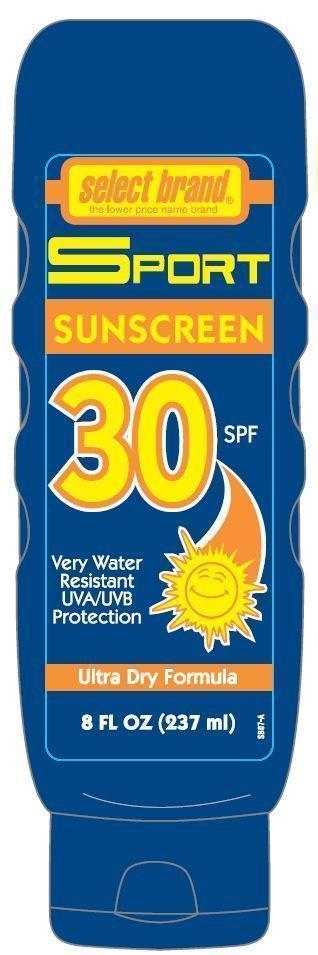 DRUG LABEL: Select Brand Sport Sunscreen
NDC: 15127-001 | Form: LOTION
Manufacturer: Select Brand Distributors
Category: otc | Type: HUMAN OTC DRUG LABEL
Date: 20121203

ACTIVE INGREDIENTS: AVOBENZONE 2 g/100 g; HOMOSALATE 10 g/100 g; OCTISALATE 5 g/100 g; OCTOCRYLENE 4 g/100 g; OXYBENZONE 5 g/100 g
INACTIVE INGREDIENTS: WATER; PROPYLENE GLYCOL; BENZYL ALCOHOL; TROLAMINE; CHLORPHENESIN; EDETATE DISODIUM; TOCOPHEROL

Drug Facts

Active ingredients

Avobenzone 2.0%
Homosalate 10.0%
Octisalate 5.0%
Octocrylene 4.0%
Oxybenzone 5.0%

Purpose

Sunscreen

Uses

- helps prevent sunburn
- higher SPF gives more sunburn protection
- retains SPF after 80 minutes of activity in water

Warnings

For external use only

When using this product

- keep out of eyes. Rinse with water to remove.

Stop use and ask a doctor if

- rash or irritation develops and lasts.

Keep out of the reach of children.
If swallowed get medical help or contact a Poison Control Center right away.

Directions

- shake well
- apply generously and evenly before sun exposure and as needed
- children under 6 months of age: ask a doctor
- reapply frequently and after towel drying, swimming or perspiring

Other information

- may stain some materials

Inactive ingredients

Water, Neopentyl Glycol Diheptanoate, Styrene/Acrylates Copolymer, Propylene Glycol, Polyglyceryl-3 Methylglucose Distearate, Benzyl Alcohol, Acrylates/C10-30 Alkyl Acrylate Crosspolymer, Triethanolamine, Disodium EDTA, Oleth-3, Tocopherol, Chlorphenesin, Fragrance.

Principal Display Panel

select brand
the lower price name brand
SPORT
SUNSCREEN
30 SPF
Very Water Resistant
UVA/UVB Protection
Ultra Dry Formula
8 FL OZ(237 mL)